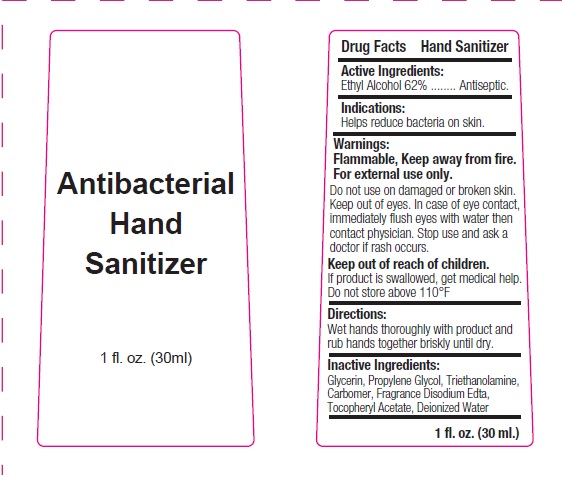 DRUG LABEL: Antibacterial HAND SANITIZER
NDC: 75613-002 | Form: GEL
Manufacturer: Ningbo Lanzi Cosmetic Technology Co., Ltd
Category: otc | Type: HUMAN OTC DRUG LABEL
Date: 20200513

ACTIVE INGREDIENTS: ALCOHOL 62 mL/100 mL
INACTIVE INGREDIENTS: WATER; PROPYLENE GLYCOL; EDETATE DISODIUM; TROLAMINE; .ALPHA.-TOCOPHEROL ACETATE, D-; GLYCERIN

HAND SANITIZER

Active ingredient

Ethyl Alcohol 62%

Purpose

Antiseptic

Use

Help reduce bacteria on skin.

Warnings

For external use only.

Flammable.Keep product away from fire or flame.

Do not use on damaged or broken skin.

Keep out of eye. In case of eye contact, immediately flush with water then contact physician.

Stop use and ask a doctor if

rash occurs.

Keep out of reach of children.

If swallowed, get medical help or contact a Poison Control Center right away.

Directions

Wet hands thoroughly with product and rub hands together briskly until dry.

Inactive ingredients

Glycerin,Propylene Glycol, Triethanolamine, Carbomer, Fragrance, Disodium Edta, Tocopheryl Acetate, Deionized Water